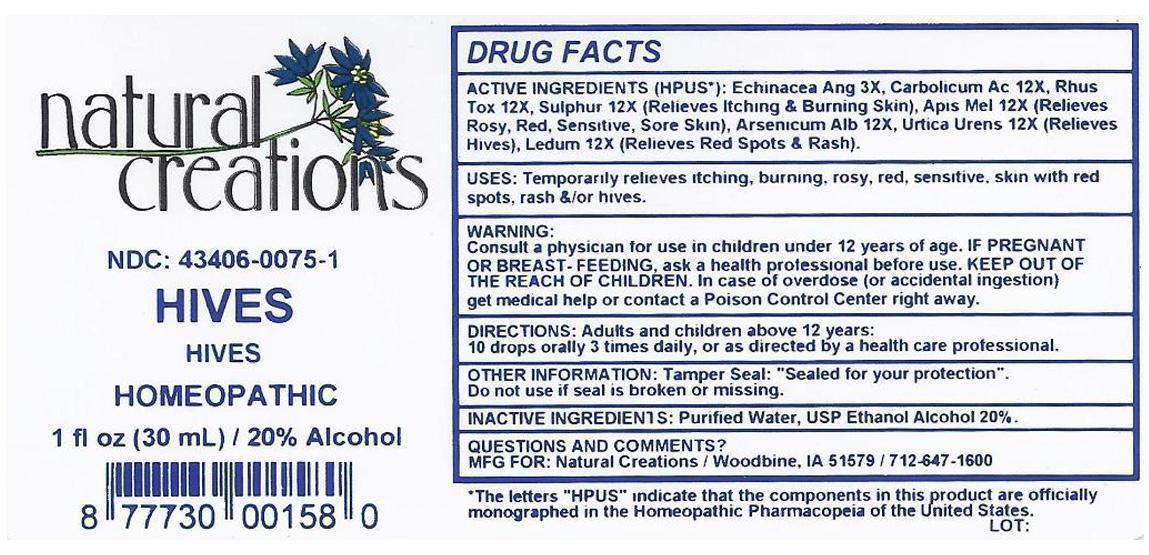 DRUG LABEL: HIVES
NDC: 43406-0075 | Form: LIQUID
Manufacturer: Natural Creationa, Inc.
Category: homeopathic | Type: HUMAN OTC DRUG LABEL
Date: 20130131

ACTIVE INGREDIENTS: ECHINACEA ANGUSTIFOLIA 3 [hp_X]/1 mL; APIS MELLIFERA 12 [hp_X]/1 mL; ARSENIC TRIOXIDE 12 [hp_X]/1 mL; PHENOL 12 [hp_X]/1 mL; LEDUM PALUSTRE TWIG 12 [hp_X]/1 mL; TOXICODENDRON PUBESCENS LEAF 12 [hp_X]/1 mL; SULFUR 12 [hp_X]/1 mL; URTICA URENS 12 [hp_X]/1 mL
INACTIVE INGREDIENTS: WATER; ALCOHOL

ACTIVE INGREDIENT

ACTIVE INGREDIENTS HPUS*): Echinacea Angustifolia 3X, Apis Mellifica 12X, Arsenicum Album 12X, Carbolicum 12X, Ledum Palustre 12X, Rhus Toxicodendron 12X, Sulphur 12X, Urtica Urens 12X

PURPOSE

USES: Temporarily relieves itching, burning, rosy, red, sensitive, skin with red spots, rash, &/or hives.

KEEP OUT OF REACH OF CHILDREN

KEEP OUT OF THE REACH OF CHILDREN. In case of overdose (or accidental ingestion) get medical help or contact a Poison Control Center.

INDICATIONS AND USAGE

Uses: Temporarily relieves itching, burning, rosy, red, sensitive, skin with red spots, rash &/or hives.

WARNING:

Consult a physican for use in children under 12 years of age. IF PREGNANT OR BREAST-FEEDING, ask a health care professional before use. KEEP OUT OF THE REACH OF CHILDREN. In case of overdose (or accidental ingestion) get medical help or contact a Poison Control Center right away.

DOSAGE AND ADMINISTRATION

DIRECTIONS: Adults and children above 12 years: 10 drops orally 3 times daily, or as directed by a health care professional.

INACTIVE INGREDIENTS: Purified Water, USP Ethanol Alcohol 20%

PACKAGE LABEL

NDC: 43406-0075-1

HIVES

HIVES

HOMEOPATHIC

1 fl oz (30 mL) / 20% Alcohol

UPC: 877730001580